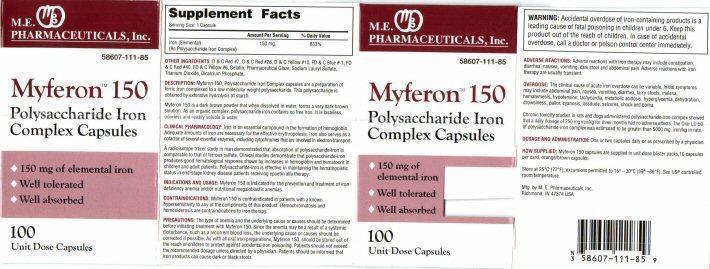 DRUG LABEL: Myferon 150
NDC: 58607-111 | Form: CAPSULE
Manufacturer: MARTIN EKWEALOR PHARMACEUTICALS, INC.
Category: otc | Type: HUMAN OTC DRUG LABEL
Date: 20140220

ACTIVE INGREDIENTS: IRON SUCROSE 150 mg/1 1
INACTIVE INGREDIENTS: D&C RED NO. 7; D&C RED NO. 28; D&C YELLOW NO. 10; FD&C BLUE NO. 1; FD&C RED NO. 40; FD&C YELLOW NO. 6; GELATIN; SHELLAC; SODIUM LAURYL SULFATE; TITANIUM DIOXIDE; CALCIUM PHOSPHATE, DIBASIC, ANHYDROUS

SUPPLEMENTAL FACTS

Serving Size: 1 Capsule

Amount Per Serving % Daily Value

Iron (Elemental) 150 mg 833%
(As Polysaccharide Iron Complex)

INDICATIONS:

prevention and treatment of iron deficiency and/or other nutritional megaloblastic anemias

WARNING: Keep this product out of reach of children.

WARNING: Accidental overdose of iron-containing products is a leading cause of fatal poisoning in children under 6. Keep this product out of the reach of children. In case of accidental overdose, call a doctor or poison control center immediately.

INDICATIONS AND USAGE:

Myferon 150 is indicated for the prevention and treatment of iron deficiency anemia and/or nutritional megaloblastic anemias.

WARNING:

WARNING: Accidental overdose of iron-containing products is a leading cause of fatal poisoning in children under 6. Keep this product out of the reach of children. In case of accidental overdose, call a doctor or poison control center immediately.

DOSAGE AND ADMINISTRATION:

One or two capsules daily or as prescribed by a physician.

Inactive Ingredients OTHER INGREDIENTS:

D and C Red #7, D and C Red #28, D and C Yellow #10, FD and C Blue #1, FD and C Red #40, FD and C Yellow #6, Gelatin, Pharmaceutical Glaze, Sodium Lauryl Sulfate, Titanium Dioxide, Dicalcium Phosphate.

DESCRIPTION:

Myferon 150, Polysaccharide Iron Complex capsules are a preparation of ferric Iron complexed to a low molecular weight polysaccharide. This polysaccharide is obtained by extensive hydrolysis of starch.

Myferon 150 is a dark brown powder that when dissolved in water, forms a very dark brown solution. As an organic complex, polysaccharide iron contains no free iron. It is tasteless, odorless and readily soluble in water.

CLINICAL PHARMACOLOGY:

Iron is an essential compound in the formation of hemoglobin. Adequate amounts of iron are necessary for the effective erythropoiesis. Iron also serves as a cofactor of several essential enzymes, including cytochromes that are involved in electron transport.

A radioiscope tracer study in man demonstrated that absorption of a polysacchride-iron is comparable to that of ferrous sulfate. Clinical studies demonstrate that polysaccharide-iron produces good hematological response shown by increases in hemoglobin and hematocrit in children and adult patients. Polysaccharide-iron is effective in maintaining the hematopoietic status in end-stage kidney disease patients receiving epoetin alfa therapy.

CONTRAINDICATIONS:

Myferon 150 is contraindicated in patients with a known hypersensitivity to any of the components of this product. Hemochromatosis and hemosiderosis are contraindications to iron therapy.

PRECAUTIONS:

The type of anemia and the underlying cause or causes should be determined before initiating treatment with Myferon 150. Since the anemia may be a result of a systemic disturbance, such as recurrent blood loss, the underlying cause or causes should be corrected if possible. As with all oral iron preparations, Myferon 150 should be stored out of the reach of children to protect against accidental iron poisoning. Patients should not exceed the recommended dosage unless directed by a physician. Patients should be informed that iron products can cause dark or black stools.

ADVERSE REACTIONS:

Adverse reactions with iron therapy may include constipation, diarrhea, nausea, vomiting, dark stool and abdominal pain. Adverse reactions with iron are usually transient.

OVERDOSE:

The clinical cause of acute iron overdose can be variable. Initial symptoms may include abdominal pain, nausea, vomiting, diarrhea, tarry stools, melena, hematemesis, hypotension, tachycardia, metabolic acidosis, hyperglycemia, dehydration, drowsiness, pallor, cyanosis, lassitude, seizures, shock and coma.

Chronic toxicity studies in rats and dogs administered polysaccharide-iron complex showed that a daily dosage of 250 mg iron/kg for three months has no adverse effects. The Oral LD 50 of polysaccharide-iron complex was estimated to be greater than 5000 mg. iron/kg in rats.

HOW SUPPLIED:

Myferon 150 capsules are supplied in unit dose blister packs, 10 capsules per card, orange/brown capsules.

Store at 25° C (77° F); excursions permitted to 15°-30° C (59°-86° F). See USP controlled room temperature.

Myferon 150 Product Label

M.E. PHARMACEUTICALS, Inc.

58607-111-85

Myferon™ 150
Polysaccharide Iron Complex Capsules

150 mg of elemental iron
Well tolerated
Well absorbed

100 Unit Dose Capsules

Mfg by M.E. Pharmaceuticals, Inc.
Richmond, IN 47374 USA